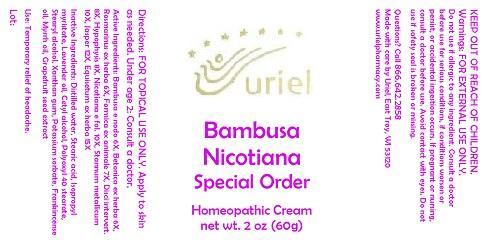 DRUG LABEL: Bambusa Nicotiana Special Order
NDC: 48951-2109 | Form: CREAM
Manufacturer: Uriel Pharmacy Inc.
Category: homeopathic | Type: HUMAN OTC DRUG LABEL
Date: 20141125

ACTIVE INGREDIENTS: BAMBUSA VULGARIS WHOLE 6 [hp_X]/1 g; STACHYS OFFICINALIS 6 [hp_X]/1 g; ROSMARINUS OFFICINALIS FLOWERING TOP 6 [hp_X]/1 g; FORMICA RUFA 7 [hp_X]/1 g; BOS TAURUS INTERVERTEBRAL DISC 8 [hp_X]/1 g; BOS TAURUS PITUITARY GLAND 8 [hp_X]/1 g; TOBACCO LEAF 10 [hp_X]/1 g; TIN 10 [hp_X]/1 g; COLLOIDAL SILICON DIOXIDE 12 [hp_X]/1 g; EQUISETUM ARVENSE TOP 15 [hp_X]/1 g
INACTIVE INGREDIENTS: WATER; STEARIC ACID; ISOPROPYL MYRISTATE; LAVENDER OIL; CETYL ALCOHOL; POLYOXYL 40 STEARATE; STEARYL ALCOHOL; XANTHAN GUM; POTASSIUM SORBATE; FRANKINCENSE OIL; MYRRH OIL; CITRUS PARADISI SEED

Bambusa Nicotiana Special Order

INDICATIONS AND USAGE

Directions: FOR TOPICAL USE ONLY.

DOSAGE AND ADMINISTRATION

Apply to skin as needed. Under age 2: Consult a doctor.

ACTIVE INGREDIENT

Active Ingredients: Bambusa e nodo 6X, Betonica ex herba 6X, Rosmarinus ex herba 6X, Formica ex animale 7X, Disci intervert. 8X, Hypophysis 8X, Nicotiana e fol. 10X, Stannum metallicum 10X, Jasper 12X, Equisetum ex herba 15X

INACTIVE INGREDIENT

Inactive Ingredients: Distilled water, Stearic acid, Isopropyl myristate, Lavender oil, Cetyl alcohol, Polyoxyl 40 stearate, Stearyl alcohol, Xanthan gum, Potassium sorbate, Frankincense oil, Myrrh oil, Grapefruit seed extract

PURPOSE

Use: Temporary relief of headache.

KEEP OUT OF REACH OF CHILDREN.

WARNINGS

Warnings: FOR EXTERNAL USE ONLY. Do not use if allergic to any ingredient. Consult a doctor before use for serious conditions, if conditions worsen or persist, or accidental ingestion occurs. If pregnant or nursing, consult a doctor before use. Avoid contact with eyes. Do not use if safety seal is broken or missing.

QUESTIONS

Questions? Call 866.642.2858 Made with care by Uriel, East Troy, WI 53120 www.urielpharmacy.com